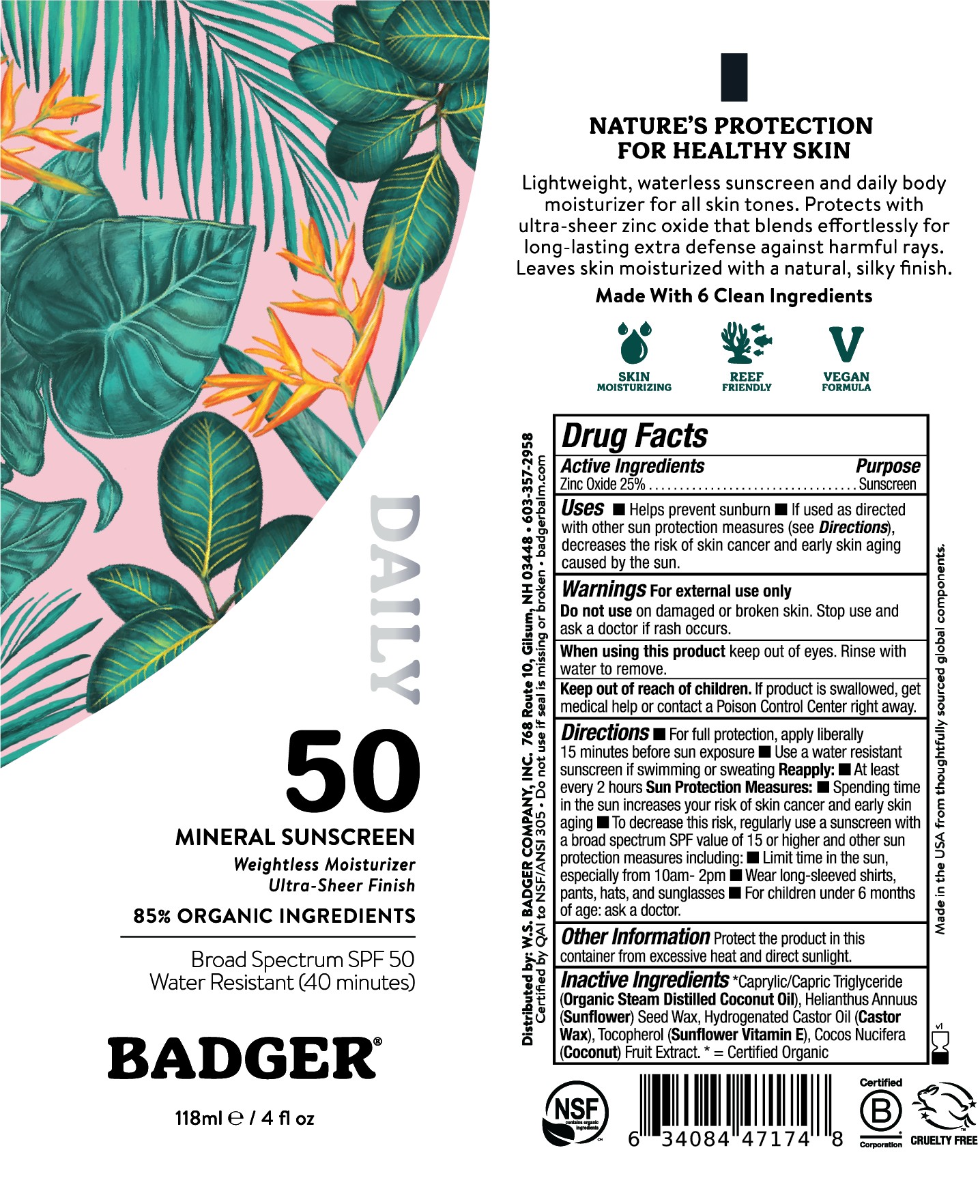 DRUG LABEL: Badger SPF 50 Daily Mineral Sunscreen
NDC: 62206-5081 | Form: CREAM
Manufacturer: W.S. Badger Company, Inc.
Category: otc | Type: HUMAN OTC DRUG LABEL
Date: 20251217

ACTIVE INGREDIENTS: ZINC OXIDE 25 g/100 mL
INACTIVE INGREDIENTS: CAPRYLIC/CAPRIC TRIGLYCERIDE; COCOS NUCIFERA (COCONUT) FRUIT; TOCOPHEROL; HELIANTHUS ANNUUS (SUNFLOWER) SEED WAX; HYDROGENATED CASTOR OIL

Badger® SPF 50 Daily MIneral Sunscreen

Drug Facts

Active Ingredient

Non-Nano Uncoated Zinc Oxide 25%

Purpose

Sunscreen

Uses

- Helps prevent sunburn
- If used as directed with other sun protection measures (see Directions), decreases the risk of skin cancer and early skin aging caused by the sun.

Warnings

For external use only

Do not use on damaged or broken skin. Stop use and ask a doctor if rash occurs.

When using this product keep out of eyes. Rinse with water to remove.

Keep out of reach of children. If product is swallowed, get medical help or contact a Poison Control Center right away.

Directions

- For full protection, apply liberally (2mg/cm^2 of skin) to all exposed skin 15 minutes before sun exposure.

Reapply:

- After 80 minutes of swimming or sweating
- Immediately after towel drying
- At least every 2 hours

Sun Protection Measures:

- Spending time in the sun increases your risk of skin cancer and early skin aging
- To decrease this risk, regularly use a sunscreen with a broad spectrum SPF value of 15 or higher and other sun protection measures including:
  - Limit time in the sun, especially from 10am-2pm
  - Wear long-sleeved shirts, pants, hats, and sunglasses
- For children under 6 months of age: ask a doctor.

Other Information

Protect the product in this container from excessive heat and direct sunlight.

Inactive Ingredients

*Caprylic/Capric Triglyceride (Organic Steam Distilled Coconut Oil), Helianthus Annuus (Sunflower) Seed Wax, Hydrogenated Castor Oil (Castor Wax), Tocopherol (Sunflower Vitamin E), Cocos Nucifera (Coconut) Fruit Extract. *= Organic

PRINCIPAL DISPLAY PANEL

BADGER ® ADVENTURE

Mineral Sunscreen Cream

Weightless Moisturizer

Ultra-Sheer Finish

85% Organic Ingredients

BROAD SPECTRUM

SPF 50

WATER RESISTANT (40 MIN)

Nature's Protection for Healthy Skin

Lightweight, waterless sunscreen and daily body moisturizer for all skin tones. Protects with ultra-sheer zinc oxide that blends effortlessly for long-lasting extra defense against harmful rays. Leaves skin moisturized with a natural, silky finish.

Made with 6 Clean Ingredients

Skin moisturizing

Reef Friendly

Vegan formulation

CRUELTY FREE

50% Recycled Package

NSF

Certified B Corporation

Cruelty Free

118ml / 4 fl oz

Made in the USA from thoughtfully sourced global components

Distributed by W.S. Badger Company, Inc. 768 Route 10, Gilsum, NH 03448 603-357-2958

Certified by QAI to NSF/ANSI 305

Do not use if seal is missing or broken

badgerbalm.com